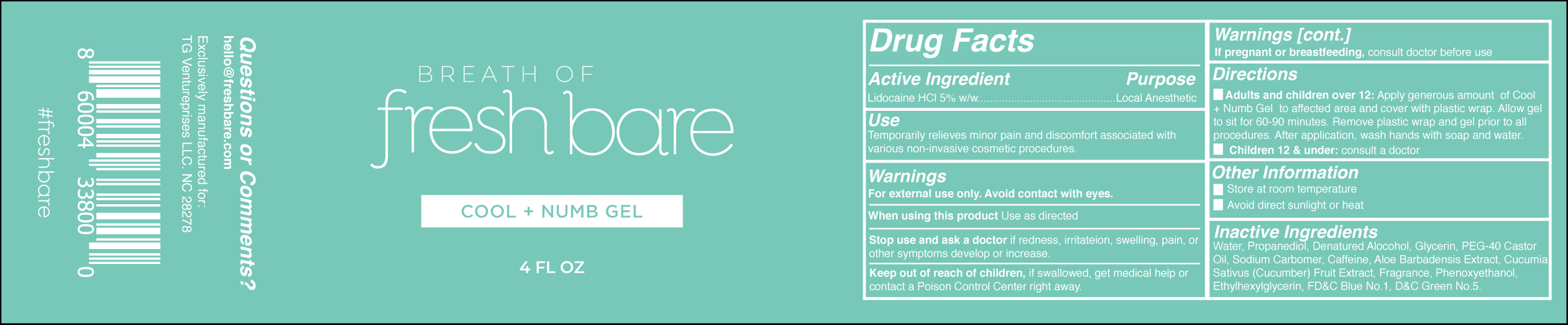 DRUG LABEL: Reg
NDC: 73663-001 | Form: GEL
Manufacturer: TG Ventureprises LLC
Category: otc | Type: HUMAN OTC DRUG LABEL
Date: 20200705

ACTIVE INGREDIENTS: LIDOCAINE 5 g/100 g
INACTIVE INGREDIENTS: ALCOHOL 4 g/100 g; CUCUMBER JUICE 0.1 g/100 g; CARBOMER 940 2 g/100 g; GLYCERIN 2 g/100 g; CAFFEINE 0.25 g/100 g; 1,3-PROPANEDIOL BIS(4-AMINOBENZOATE) 5 g/100 g; ALOE VERA LEAF 0.2 g/100 g

Numb Gel 5%